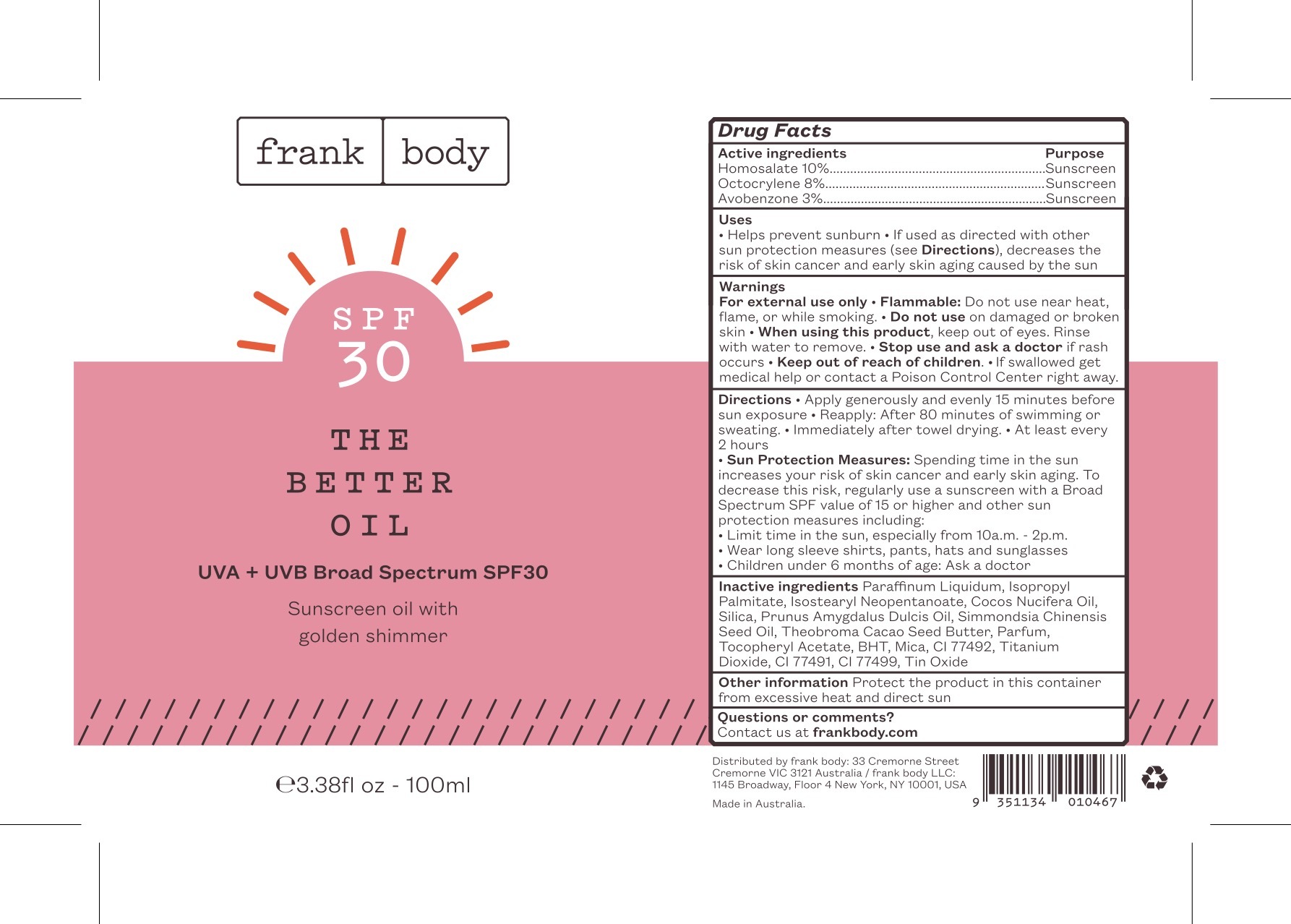 DRUG LABEL: UVA and UVB Broad Spectrum SPF30 Sunscreen Oil with golden shimmer
NDC: 70157-008 | Form: OIL
Manufacturer: Baxter Laboratories Pty. Ltd.
Category: otc | Type: HUMAN OTC DRUG LABEL
Date: 20241018

ACTIVE INGREDIENTS: HOMOSALATE 10 g/100 mL; OCTOCRYLENE 8 g/100 mL; AVOBENZONE 3 g/100 mL
INACTIVE INGREDIENTS: COCOA BUTTER; STANNIC OXIDE; JOJOBA OIL; SILICON DIOXIDE; .ALPHA.-TOCOPHEROL ACETATE; ISOPROPYL PALMITATE; ISOSTEARYL NEOPENTANOATE; COCONUT OIL; MICA; FERROSOFERRIC OXIDE; FERRIC OXIDE YELLOW; MINERAL OIL; TITANIUM DIOXIDE; BUTYLATED HYDROXYTOLUENE; ALMOND OIL; FERRIC OXIDE RED

UVA and UVB Broad Spectrum SPF30 Sunscreen Oil with golden shimmer

Active ingredients Purpose

Homosalate 10% ..................Sunscreen

Octocrylene 8% ....................Sunscreen

Avobenzone 3% ...................Sunscreen

Uses

- Helps prevent sunburn
- If used as directed with other sun protection measures (see Directions), decreases the risk of skin cancer and early skin aging caused by the sun

Keep out of reach of children.

Stop use and ask a doctor if rash occurs

WARNINGS

For external use only

- Flammable: Do not use near heat, flame, or while smoking
- Do not use on damaged or broken skin
- When using this product, keep out of eyes. Rinse with water to remove.
- If swallowed get medical help or contact a Poison Control Center right away.

Directions

- Apply generously and evenly 15 minutes before sun exposure
- Reapply: After 80 minutes of swimming or sweating
- Immediately after towel drying
- At least every 2 hours
- Sun Protection Measures: Spending time in the sun increases your risk of skin cancer and early skin aging. To decrease this risk, regularly use a sunscreen with a Broad Spectrum SPF value of 15 or higher and other sun protection measures including:
- Limit time in the sun, espicially from 10a.m.-2p.m.
- Wear long sleeve shirts, pants, hats and sunglasses
- Children under 6 months of age: Ask a doctor

Inactive ingredients

Paraffinum Liquidum, Isopropyl Palmitate, Isostearyl Neopentanoate, Cocos Nucifera Oil, Silica, Prunus Amygdalus Dulcis Oil, Simmondsia Chinensis Seed Oil, Theobroma Cacao Seed Butter, Parfum, Tocopheryl Acetate, BHT, Mica, CI 77492, Titanium Dioxide, CI 77491, CI 77499, Tin Oxide

Other information Protect the product in this container from excessive heat and direct sun

PACKAGE LABEL

frank body

SPF 30

THE BETTER OIL

UVA + UVB Broad Spectrum SPF30

Sunscreen oil with golden shimmer

3.38fl oz - 100ml